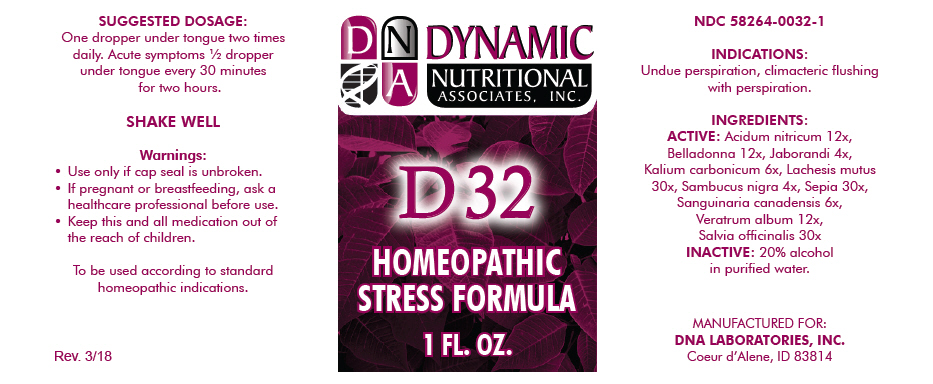 DRUG LABEL: D-32
NDC: 58264-0032 | Form: SOLUTION
Manufacturer: DNA Labs, Inc
Category: homeopathic | Type: HUMAN OTC DRUG LABEL
Date: 20250113

ACTIVE INGREDIENTS: NITRIC ACID 12 [hp_X]/1 mL; ATROPA BELLADONNA 12 [hp_X]/1 mL; PILOCARPUS JABORANDII WHOLE 4 [hp_X]/1 mL; POTASSIUM CARBONATE 6 [hp_X]/1 mL; LACHESIS MUTA VENOM 30 [hp_X]/1 mL; SAMBUCUS NIGRA FLOWERING TOP 4 [hp_X]/1 mL; SEPIA OFFICINALIS JUICE 30 [hp_X]/1 mL; SANGUINARIA CANADENSIS ROOT 6 [hp_X]/1 mL; VERATRUM ALBUM ROOT 12 [hp_X]/1 mL; SAGE 30 [hp_X]/1 mL
INACTIVE INGREDIENTS: ALCOHOL; WATER

D-32

NDC 58264-0032-1

INDICATIONS

PURPOSE

Undue perspiration, climacteric flushing with perspiration.

INGREDIENTS

ACTIVE

Acidum nitricum 12x, Belladonna 12x, Jaborandi 4x, Kalium carbonicum 6x, Lachesis mutus 30x, Sambucus nigra 4x, Sepia 30x, Sanguinaria canadensis 6x, Veratrum album 12x, Salvia officinalis 30x

INACTIVE

20% alcohol in purified water.

SUGGESTED DOSAGE

One dropper under tongue two times daily. Acute symptoms ½ dropper under tongue every 30 minutes for two hours.

STORAGE AND HANDLING

SHAKE WELL

Warnings

- Use only if cap seal is unbroken.

PREGNANCY OR BREAST FEEDING

- If pregnant or breastfeeding, ask a healthcare professional before use.

KEEP OUT OF REACH OF CHILDREN

- Keep this and all medication out of the reach of children.

To be used according to standard homeopathic indications.

PRINCIPAL DISPLAY PANEL - 1 FL. OZ. Bottle Label

DYNAMIC
NUTRITIONAL
ASSOCIATES, INC.

D 32

HOMEOPATHIC
STRESS FORMULA

1 FL. OZ.